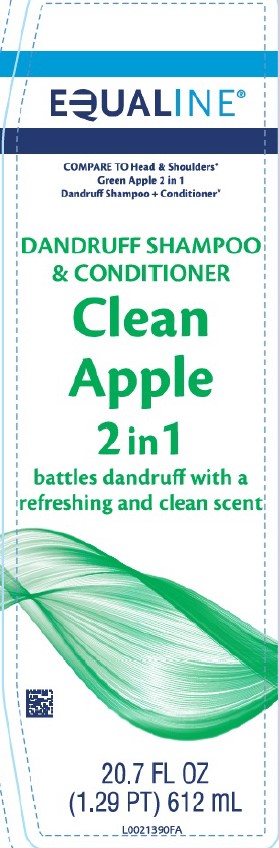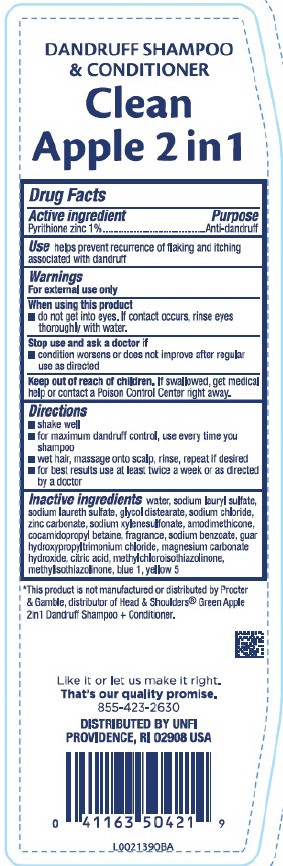 DRUG LABEL: 2 in 1 Dandruff
NDC: 41163-266 | Form: SHAMPOO
Manufacturer: United Natural Foods, Inc. dba UNFI
Category: otc | Type: HUMAN OTC DRUG LABEL
Date: 20260217

ACTIVE INGREDIENTS: PYRITHIONE ZINC 10 mg/1 mL
INACTIVE INGREDIENTS: WATER; SODIUM LAURYL SULFATE; SODIUM LAURETH SULFATE; GLYCOL DISTEARATE; SODIUM CHLORIDE; ZINC CARBONATE; SODIUM XYLENESULFONATE; AMODIMETHICONE (800 CST); COCAMIDOPROPYL BETAINE; SODIUM BENZOATE; GUAR HYDROXYPROPYLTRIMONIUM CHLORIDE (1.7 SUBSTITUENTS PER SACCHARIDE); MAGNESIUM CARBONATE HYDROXIDE; CITRIC ACID MONOHYDRATE; METHYLCHLOROISOTHIAZOLINONE; METHYLISOTHIAZOLINONE; FD&C BLUE NO. 1; FD&C YELLOW NO. 5

Equaline 612.001/612AC-AE
Clean Apple Dandruff Shampoo and Conditioner

Claims

DANDRUFF SHAMPOO & CONDITIONER

Clean

Apple 2in1

Active ingredient

Pyrithione zinc 1%

Purpose

Anti-dandruff

Use

helps prevent recurrence of flaking and itching associated with dandruff

Warnings

For external use only

When using this product

- do not get into eyes. If contact occurs, rinse eyes thoroughly with water.

Stop use and ask a doctor if

- condition worsens or does not improve after regular use as directed

Keep out of reach of children.

If swallowed, get medical help or contact a Poison Control Center right away.

Directions

- shake well
- for maximum dandruff control, use every time you shampoo
- wet hair, massage onto scalp, rinse, repeat if desired
- for best results use at least twice a week or as directed by a doctor

Inactive ingredients

water, sodium lauryl sulfate, sodium laureth sulfate, glycol distearate, sodium chloride, zinc carbonate, sodium xylenesulfonate, amodimethicone, cocamidopropyl betaine, fragrance, sodium benzoate, guar hydroxypropyltrimonium chloride, magnesium carbonate hydroxide, citric acid, methylchloroisothiazolinone, methylisothiazolinone, blue 1, yellow 5

Disclaimer

*This product is not manufactured or distributed by Procter & Gamble, distributor of Head & Shoulder® Green Apple 2in1 Dandruff Shampoo + Conditioner.

Adverse reaction

Like it or let us make it right.

That's our quality promise.

855-423-2630

DISTRIBUTED By UNFI

PROVIDENCE, RI 02908 USA

Principal display panel

EQUALINE®

COMPARE TO Head & Shoulders® Green Apple 2 in 1 Dandruff Shumpoo + Conditioner*

DANDRUFF SHAMPOO

& CONDITIONER

Clean

Apple

2in1

battles dandruff with a refreshing and clean scent

20.7 FL OZ (1.29 PT) 612 mL